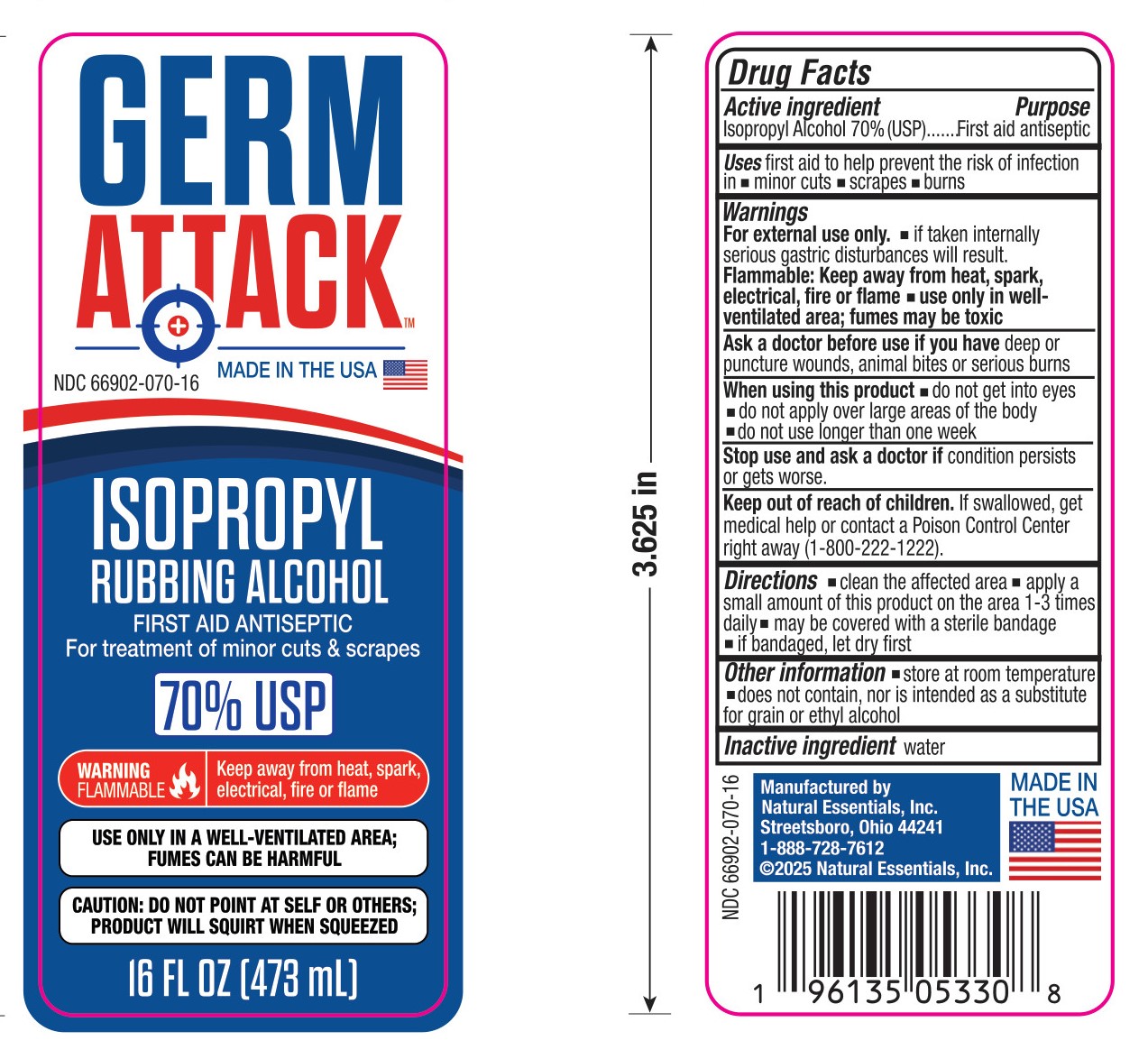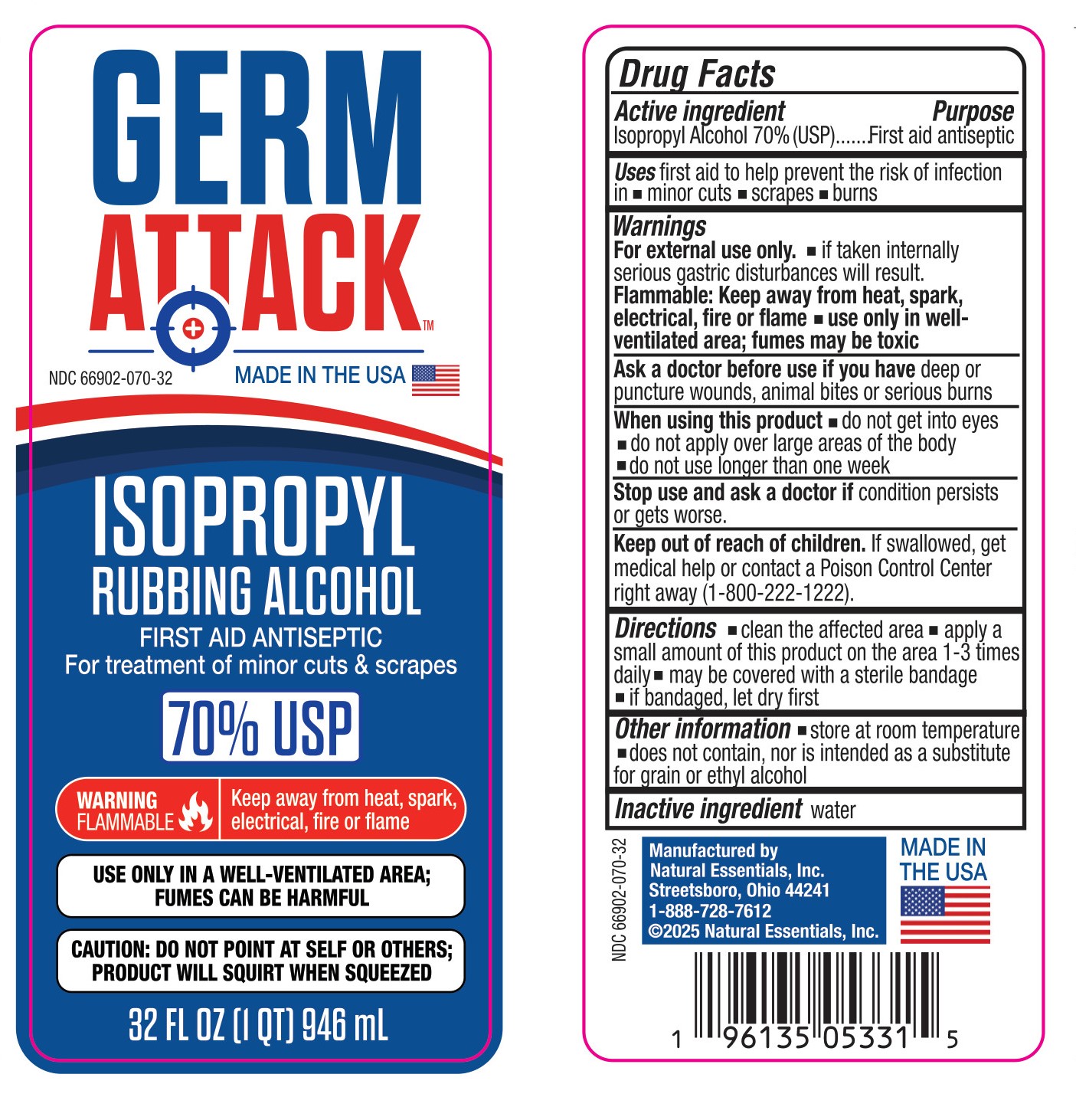 DRUG LABEL: Germ Attack 70% Isopropyl Alcohol
NDC: 66902-070 | Form: LIQUID
Manufacturer: Natural Essentials, Inc.
Category: otc | Type: HUMAN OTC DRUG LABEL
Date: 20250425

ACTIVE INGREDIENTS: ISOPROPYL ALCOHOL 0.7 mL/1 mL
INACTIVE INGREDIENTS: WATER

Germ Attack 70% Isopropyl Alcohol

Active Ingredient

Isopropyl Alcohol 70% (USP)

Purpose

First aid antiseptic

Uses

first aid to help prevent the risk of infection in

- minor cuts
- scrapes
- burns

Warnings

For external use only.

- If taken internally serious gastric disturbances will result.

Flammable: Keep away from heat, spark, electrical, fire or flame

- Use only in well-ventilated area; fumes may be toxic

Ask a doctor before use if you have

deep or puncture wounds, animal bites or serious burns

When using this product

- do not get into eyes
- do not apply over large areas of the body
- do not use longer than one week

Stop use and ask a doctor if

condition persists or gets worse

Keep out of reach of children.

If swallowed, get medical help or contact a Posion Control Center right away (1-800-222-1222).

Directions

- clean the affected area
- apply a small amount of this product on the area 1-3 times daily
- may be covered with a sterile bandage
- if bandaged, let dry first

Other information

- store at room temperature
- does not contain, nor is intended as a substitute for grain or ethyl alcohol

Inactive ingredient

water

Principal Display Panel - 16 fl. oz.

Germ AttackTM

Made in the USA

NDC 66902-070-16

Isopropyl Rubbing Alcohol

First Aid Antiseptic

For the treatment of minor cuts & scrapes

70% USP

Warning

Flammable

Keep away from heat, spark, electrical, fire, or flame

Use only in a well-ventilated area; fumes can be harmful

Caution: Do not point at self or others; product will squirt when squeezed

16 fl. oz (473 mL)

Principal Display Panel - 32 fl. oz.

Germ AttackTM

Made in the USA

NDC 66902-070-32

Isopropyl Rubbing Alcohol

First Aid Antiseptic

For treatment of minor cuts & scrapes

70% USP

Warning

Flammable

Keep away from heat, spark, electrical, fire or flame

Use only in a well-ventilated area; fumes can be harmful

Caution: Do not point at self or others; product will squirt when squeezed

32 fl. oz. (1 qt.) 946 mL